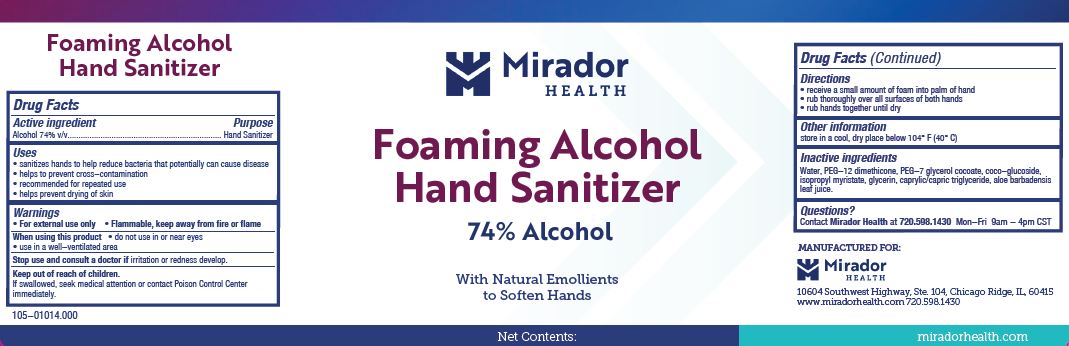 DRUG LABEL: Mirador Health Foaming Alcohol Hand Sanitizer
NDC: 59900-757 | Form: LIQUID
Manufacturer: Best Sanitizers, Inc.
Category: otc | Type: HUMAN OTC DRUG LABEL
Date: 20240111

ACTIVE INGREDIENTS: ALCOHOL 74 mL/100 mL
INACTIVE INGREDIENTS: ALOE VERA LEAF; GLYCERIN; MEDIUM-CHAIN TRIGLYCERIDES; PEG-7 GLYCERYL COCOATE; COCO-GLUCOSIDE; ISOPROPYL MYRISTATE; WATER; PEG-12 DIMETHICONE

Active ingredient

Alcohol 74% v/v

Purpose

Hand Sanitizer

Uses

- santizes hands to help reduce bacteria that potentially can cause disease
- helps to prevent cross-contamination
- recommended for repeated use
- helps prevent drying of skin

Warnings

- For external use only
- Flammable, keep away from fire or flame

When using this product

- do not use in or near eyes
- use in a well-ventilated area

Stop use and consult a doctor if irritation or redness develop.

Keep out of reach of children.

If swallowed, seek medical attention or contact Poison Control Center immediately.

Directions

- receive a small amount of foam into palm of hand
- rub thoroughly over all surfaces of both hands
- rub hands together until dry

Other information

store in a cool, dry place below 104°F (40°C)

Inactive ingredients

Water, PEG-12 dimethicone, PEG-7 glycerol cocoate, coco-glucoside, isopropyl myristate, glycerin, caprylic/capric triglyceride, aloe barbadensis leaf juice.

Questions?

Contact Mirador Health at 720.5981430 Mon-Fri 9am-4pm CST

PACKAGE LABEL

Mirador

Health

Foaming Alcohol

Hand Sanitizer

74% Alcohol

With Natural Emollients

to Soften Hands

Net Contents: